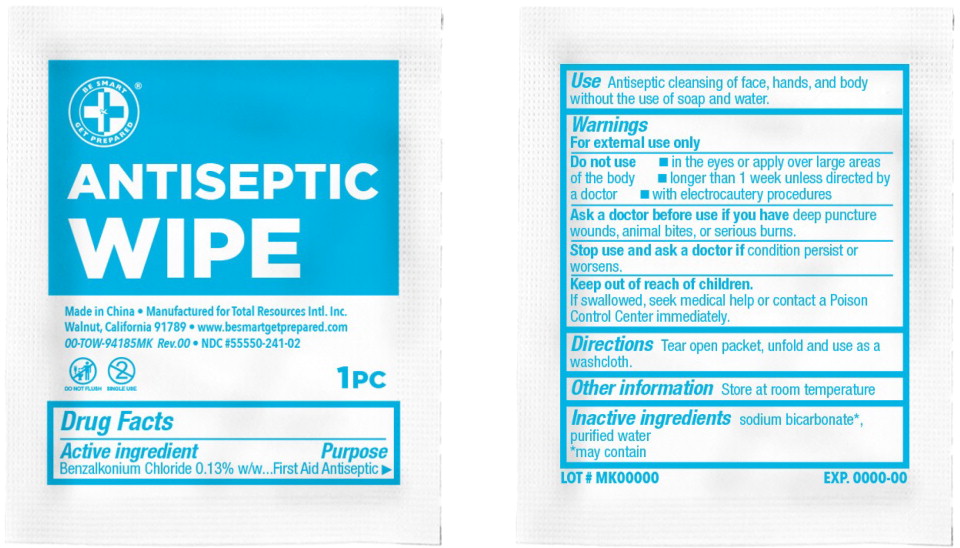 DRUG LABEL: Be Smart Get Prepared Antiseptic Wipe
NDC: 55550-241 | Form: CLOTH
Manufacturer: Total Resources International, Inc
Category: otc | Type: HUMAN OTC DRUG LABEL
Date: 20250411

ACTIVE INGREDIENTS: BENZALKONIUM CHLORIDE 1.3 mg/1 1
INACTIVE INGREDIENTS: WATER; SODIUM BICARBONATE

DRUG FACTS

Active Ingredient

- Benzalkonium Chloride 0.13% w/w…………………………………

Purpose

- First Aid Antiseptic

USE

- Antiseptic cleansing of face, hands, and body without the use of soap and water

WARNINGS

- For external use only

- Do not use
  - In eyes or apply over large areas of the body
  - Longer than 1 week unless directed by a doctor
  - With electrocautery procedures

- Ask a doctor before use if you have deep puncture wounds, animal bites, or serious burns

- Stop use and ask a doctor if condition persist or worsens

- Keep out of reach of children
  - If swallowed, get medical help or contact a Poison Control Center immediately.

DIRECTIONS

- Tear open packet, unfold and use as a washcloth

OTHER INFORMATION

- Store at room temperature

INACTIVE INGREDIENTS

- Sodium bicarbonate*, purified water

*may contain

Principal Display Panel

BE SMART

GET PREPARED®

ANTISEPTIC WIPE

Single Use

Do Not Flush

1pc

Made in China

Manufactured for Total Resources Intl. Inc.

Walnut, California 91789

www.besmartgetprepared.com • 00-TOW-94185MK Rev. 00

NDC 55550-241-02